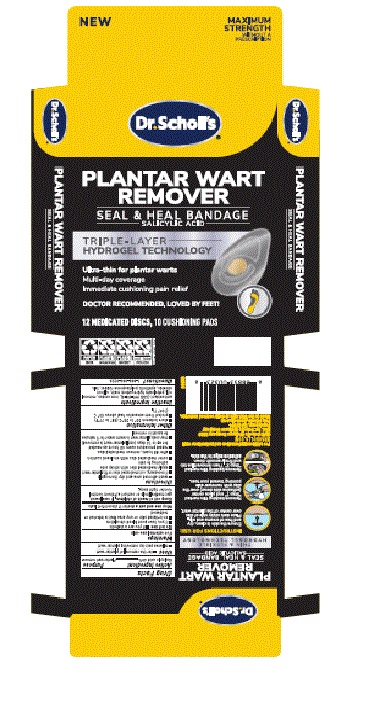 DRUG LABEL: Plantar Wart Removers
NDC: 73469-6331 | Form: DISC
Manufacturer: Scholls Wellness Company LLC
Category: otc | Type: HUMAN OTC DRUG LABEL
Date: 20251221

ACTIVE INGREDIENTS: SALICYLIC ACID 0.4 g/1 g
INACTIVE INGREDIENTS: BROWN IRON OXIDE; SILICON DIOXIDE; MINERAL OIL; ANTIOXIDANT GS; TALC; WHITE PETROLATUM

(90000386) Heal & Seal Plantar Wart Removers

Active Ingredient

Salicylic acid 40%

Purpose

Plantar Wart Remover

INDICATIONS AND USAGE

- for the removal of plantar wart
- relieves pain by removing plantar wart

WARNINGS

For external use only

DO NOT USE

- if you are a diabetic
- if you have poor blood circulation
- on irritated skin or any aea that is infected or reddened

Stop use and ask a doctor if discomfort lasts

Keep out of reach of children.

If swallowed, get medical help or contact a Poison Control Center right away

DOSAGE AND ADMINISTRATION

- wash affected area and dry thoroughly
- if necessary, cut medicated disc to fit plantar wart
- apply medicated disc with sticky side adhering to skin
- covr medicated dosc with enclosed cushion
- after 48 hours, remove medicated disc
- repeat procedure every 48 hours as needed for up to 14 days (until plantar wart is removed)
- may soak plantar wart in warm water for 5 minutes to assist in removal

STORAGE AND HANDLING

- store between 20° to 25°C (68° to 77°F)
- protect from excessive heat and temperatures above 40°C (140°F)

Inactive ingredients

Antioxidant (CAS 991-84-4), iron oxides, mineral oil, petroleum hydrocarbon resin, silicon dioxide, synthetic polyisoprene rubber, talc

Questions?

1-866-360-3226